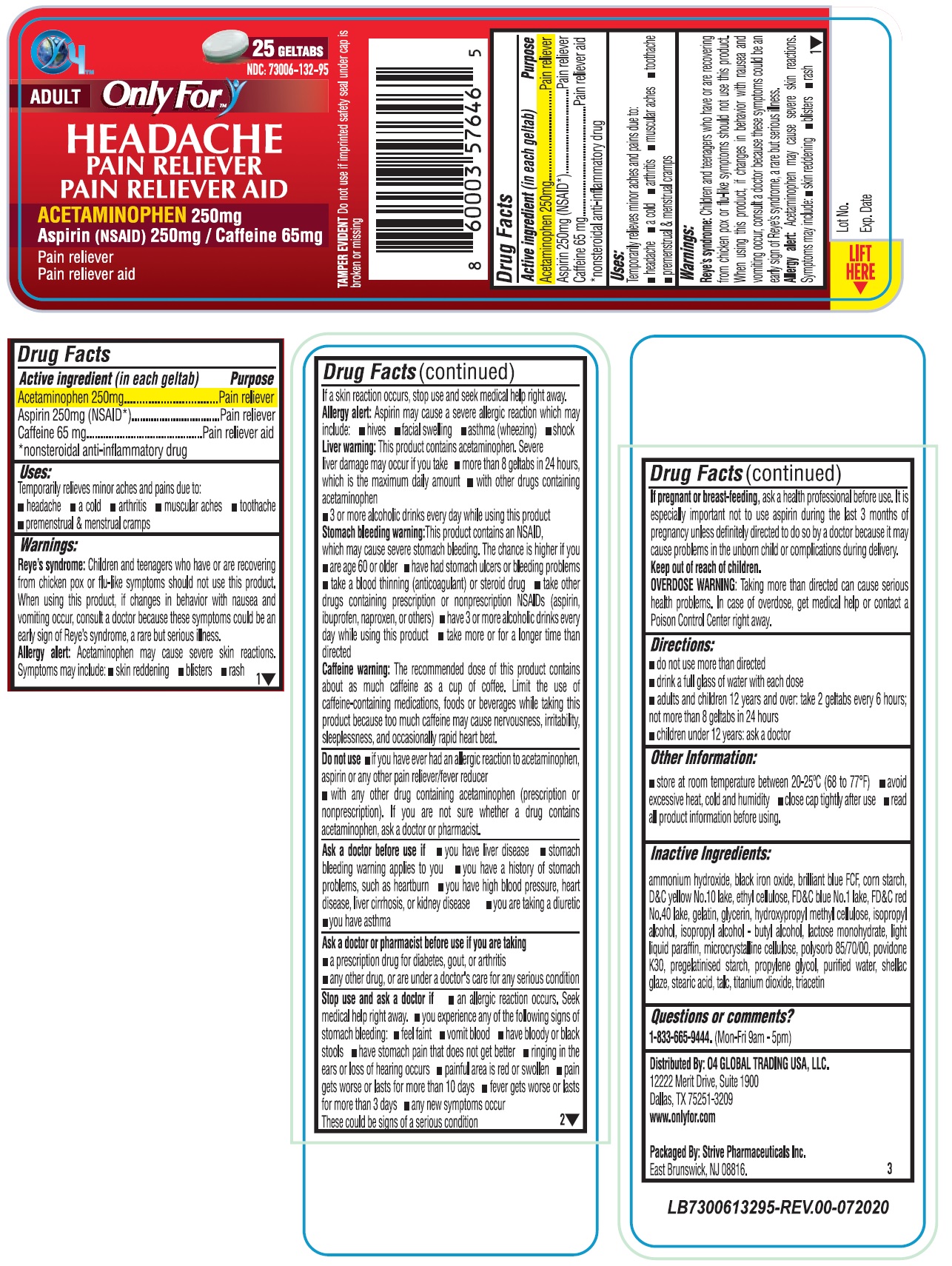 DRUG LABEL: ONLY FOR HEADACHE
NDC: 73006-132 | Form: TABLET
Manufacturer: O4 Global Trading Usa, Llc
Category: otc | Type: HUMAN OTC DRUG LABEL
Date: 20201118

ACTIVE INGREDIENTS: ACETAMINOPHEN 250 mg/1 1; ASPIRIN 250 mg/1 1; CAFFEINE 65 mg/1 1
INACTIVE INGREDIENTS: AMMONIA; FERROSOFERRIC OXIDE; FD&C BLUE NO. 1; STARCH, CORN; D&C YELLOW NO. 10; ETHYLCELLULOSE, UNSPECIFIED; FD&C RED NO. 40; GELATIN; GLYCERIN; HYPROMELLOSES; ISOPROPYL ALCOHOL; BUTYL ALCOHOL; LACTOSE MONOHYDRATE; LIGHT MINERAL OIL; MICROCRYSTALLINE CELLULOSE; SORBITOL SOLUTION; POVIDONE, UNSPECIFIED; PROPYLENE GLYCOL; WATER; SHELLAC; STEARIC ACID; TALC; TITANIUM DIOXIDE; TRIACETIN

Only For™ HEADACHE

Active ingredient (in each geltab)

Acetaminophen 250mg

Aspirin 250mg (NSAID*)

Caffeine 65 mg

*nonsteroidal anti-inflammatory drug

Purpose

Pain reliever

Pain reliever

Pain reliever aid

Uses:

Temporarily relieves minor aches and pains due to:

• headache • a cold • arthritis • muscular aches • toothache • premenstrual & menstrual cramps

Warnings:

Reye's syndrome: Children and teenagers who have or are recovering from chicken pox or flue-like symptoms should not use this product. When using this product, if changes in behavior with nausea and vomiting occur, consult a doctor because these symptoms could be an early sign of Reye's syndrome, a rare but serious illness.

Allergy alert: Acetaminophen may cause severe skin reactions. Symptoms may include: • skin reddening • blisters • rash

If a skin reaction occurs, stop use and seek medical help right away.

Allergy alert: Aspirin may cause a severe allergic reaction which may include: • hives • facial swelling • asthma (wheezing) • shock

Liver warning: This product contains acetaminophen. Severe liver damage may occur if you take • more than 8 geltabs in 24 hours, which is the maximum daily amount • with other drugs containing acetaminophen • 3 or more alcoholic drinks every day while using this product

Stomach bleeding warning: This product contains an NSAID, which may cause severe stomach bleeding. The chance is higher if you • are age 60 or older • have had stomach ulcers or bleeding problems • take a blood thinning (anticoagulant) or steroid drug • take other drugs containing prescription or nonprescription NSAIDs (aspirin, ibuprofen, naproxen or others) • have 3 or more alcoholic drinks every day while using this product • take more or for a longer time than directed

Caffeine warning: The recommended dose of this product contains about a much caffeine as cup of coffee. Limit the use of caffeine-containing medications, foods or beverages while taking this product because too much caffeine may cause nervousness, irritability, sleeplessness, and occasionally rapid heart beat.

Do not use • if you have ever had an allergic reaction to acetaminophen, aspirin or any other pain reliever/fever reducer • with any other drug containing acetaminophen (prescription or nonprescription). If you are not sure whether a drug contains acetaminophen, ask a doctor or pharmacist.

Ask a doctor before use if • you have liver disease • stomach bleeding warning applies to you • you have a history of stomach problems, such as heartburn • you have high blood pressure, heart disease, liver cirrhosis, or kidney disease • you are taking a diuretic • you have asthma

Ask a doctor or pharmacist before use if you are taking

• a prescription drug for diabetes, gout, or arthritis

• any other drug, or are under a doctor's care for any serious condition

Stop use and ask a doctor if • an allergic reaction occurs. Seek medical help right away. • you experience any of the following signs of stomach bleeding: • feel faint • vomit blood • have bloody or black stools • have stomach pain that does not get better • ringing in the ears or loss of hearing occurs • painful area is red or swollen • pain gets worse or lasts for more than 10 days • fever gets worse or lasts for more than 3 days • any new symptoms occur

These could be signs of a serious condition

If pregnant or breast-feeding, ask a health professional before use. It is especially important not to use aspirin during the last 3 months of pregnancy unless definitely directed to do so by a doctor because it may cause problems in the unborn child or compliments during delivery.

Keep out of reach of children.

OVERDOSE WARNING: Taking more than directed can cause serious health problems. In case overdose. get medical help or contact a Poison Control Center right away.

Directions:

• do not use more than directed

• drink a full glass of water with each dose

• adults and children 12 years and over: take 2 geltabs every 6 hours; not more than 8 geltabs in 24 hours

• children under 12 years: ask a doctor

Other Information:

• store at room temperature between 20-25°C (68 to 77°F) • avoid excessive heat, cold and humidity • close cap tightly after use • read all product information before using.

Inactive Ingredients:

ammonium hydroxide, black iron oxide, brilliant blue FCF, corn starch, D&C yellow No.10 lake, ethyl cellulose, FD&C blue No.1 lake, FD&C red No.40 lake, gelatin, glycerin, hydroxypropyl methyl cellulose, isopropyl alcohol, isopropyl alcohol - butyl alcohol, lactose monohydrate, light liquid paraffin, microcrystalline cellulose, polysorb 85/70/00, povidone K30, pregelatinised starch, propylene glycol, purified water, shellac glaze, stearic acid, talc, titanium dioxide, triacetin

Questions or comments?

1-833-665-9444. (Mon-Fri 9am-5pm)

ADULT

PAIN RELIEVER

PAIN RELIEVER AID

TAMPER EVIDENT: Do not use if imprinted safety seal under cap is broken or missing

Distributed By: O4 GLOBAL TRADING USA, LLC.

12222 Merit Drive, Suite 1900

Dallas, TX 75251-3209

www.onlyfor.com

Packaged By: Strive Pharmaceuticals Inc.

East Brunswick, NJ 08816.